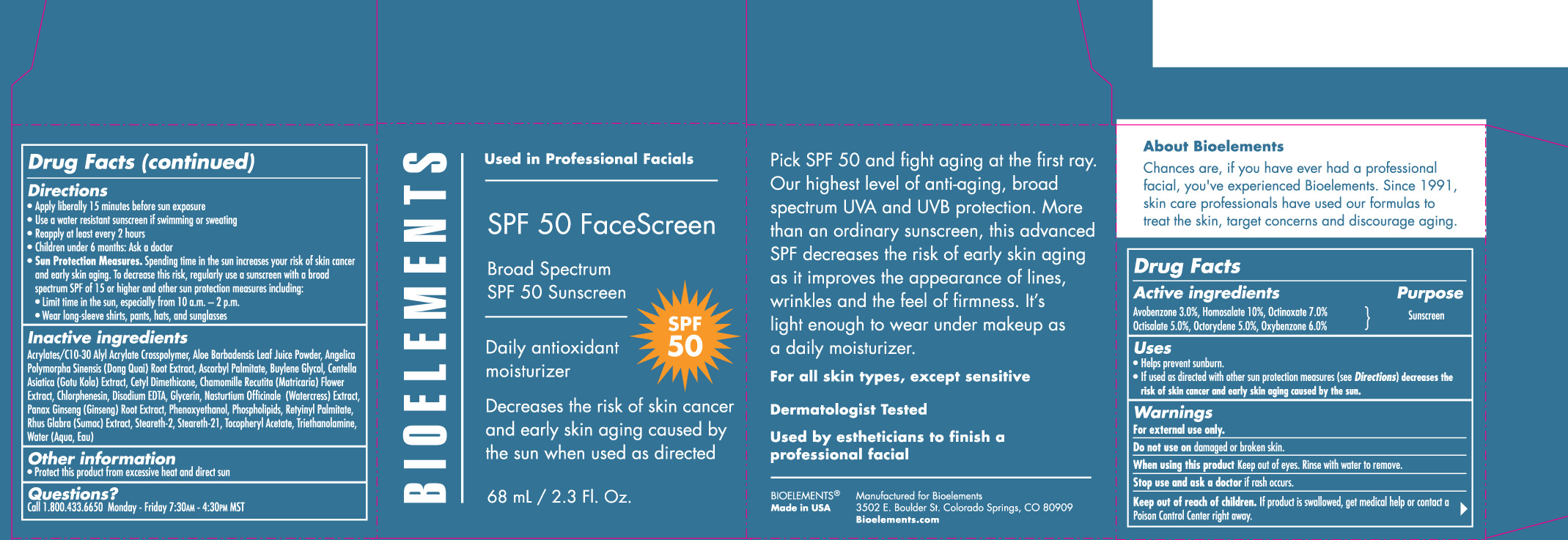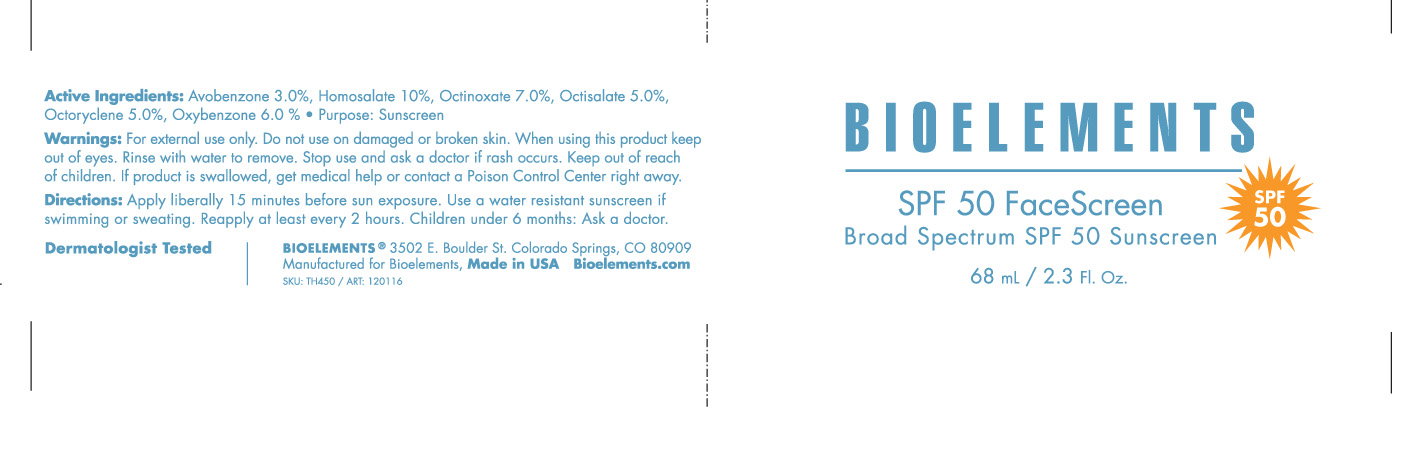 DRUG LABEL: Facescreen
NDC: 49825-122 | Form: LIQUID
Manufacturer: Bioelements
Category: otc | Type: HUMAN OTC DRUG LABEL
Date: 20120326

ACTIVE INGREDIENTS: AVOBENZONE 3.0 mL/100 mL; HOMOSALATE 10 mL/100 mL; OCTINOXATE 7.0 mL/100 mL; OCTISALATE 5.0 mL/100 mL; OCTOCRYLENE 5.0 mL/100 mL; OXYBENZONE 6.0 mL/100 mL
INACTIVE INGREDIENTS: CARBOMER INTERPOLYMER TYPE A (55000 MPA.S); ALOE VERA LEAF; ANGELICA SINENSIS ROOT; ASCORBYL PALMITATE; BUTYLENE GLYCOL; CENTELLA ASIATICA; CHAMOMILE; CHLORPHENESIN; EDETATE DISODIUM; GLYCERIN; ASIAN GINSENG; PHENOXYETHANOL; VITAMIN A PALMITATE; RHUS GLABRA BARK; STEARETH-2; STEARETH-21; ALPHA-TOCOPHEROL ACETATE; TROLAMINE; WATER

SPF 50 FaceScreen

Active ingredients Purpose

Avobenzone 3.0% Sunscreen

Homosalate 10% Sunscreen

Octinoxate 7.0% Sunscreen

Octisalate 5.0% Sunscreen

Octocrylene 5.0% Sunscreen

Oxybenzone 6.0% Sunscreen

Uses

Helps prevent sunburn

If used as directed with other sun protection measures (see Directions) decreases the risk of skin cancer and early skin aging caused by the sun.

Keep out of reach of children. If product is swallowed, get medical help or contact a Poison Control Center right away.

Stop use and ask a doctor if rash occurs

Warnings

For external use only

Do not use on broken or damaged skin

When using this product Keep out of eyes. Rinse with water to remove.

Directions

Apply liberally 15 minutes before sun exposure

Use a water resistant sunscreen if swimming or sweating

Reapply at least every 2 hours

Children under 6 months: Ask a doctor

Sun Protection Measures. Spending time in the sun increases your risk of skin cancer and early skin aging. To Decrease this risk, regularly use a sunscreen with a broad spectrum SPF of 15 or higher and other sun protection measures including

Limit time in the sun, especially from 10 a.m. - 2 p.m.

wear long-sleeve shirts, pants, hats, and sunglasses

INACTIVE INGREDIENT

Acrylates/C10-30 Alyl Acrylate Crosspolymer, Aloe Barbadensis Leaf Juice Powder, Angelica Polymorpha Sinensis (Dong Quai) Root Extract, Ascorbyl Palmitate, Butylene Glycol, Centella Asiatica (Gotu Kola) Extract, Cetyl Dimethicone, Chamomile Recutita (Matricaria) Flower Extract, Chlorphenesin, Disodium EDTA, Glycerin, Nastartium Officinale (Watercress) Extract, Panax Ginseng (Ginseng) Root Extract, Phenoxyethanol, Phospholipids, Retinyl Palmitate, Rhus Glabra (Sumac) Extract, Steareth-2, Steareth-21, Tocopheryl Acetate, Triethanolamine, Water (Aqua,Eau)

PACKAGE LABEL

Bioelements

SPF 50 FaceScreen

Broad Spectrum SPF 50 Sunscreen

68 mL/ 2.3 Fl. Oz.